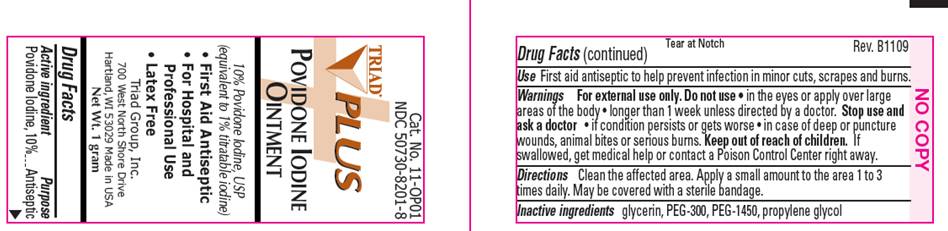 DRUG LABEL: Povidone Iodine Plus
NDC: 50730-8201 | Form: OINTMENT
Manufacturer: H and P Industries, Inc. dba Triad Group
Category: otc | Type: HUMAN OTC DRUG LABEL
Date: 20091130

ACTIVE INGREDIENTS: povidone-iodine .10 g/1 g
INACTIVE INGREDIENTS: glycerin; polyethylene glycol 300; polyethylene glycol 1450; propylene glycol

DRUG FACTS

ACTIVE INGREDIENT

Povidone Iodine USP 10% (equivalent to 1% titratable iodine)

PURPOSE

Antiseptic

USE

First Aid Antiseptic to help prevent infection in minor cuts, scrapes and burns

WARNINGS

For external use only.

Do not use

- in the eyes or over large areas of the body
- longer than 1 week unless directed by a doctor

Stop use and ask a doctor

- if condition persists or gets worse
- in case of deep puncture wounds, animal bites or serious burns

Keep out of reach of children

If swallowed, get medical help or contact a Poison Control Center right away.

DIRECTIONS

Clean the affected area. Apply a small amount of this product to the area 1-3 times daily. May be covered with a sterile bandage.

OTHER INFORMATION

Store at room temperature 15° - 30° C (59° - 86° F)

INACTIVE INGREDIENTS

glycerin, PEG-300, PEG-1450, propylene glycol

PACKAGE INFORMATION

TRIAD
Cat. No. 11-OP01
NDC 50730-8201-8
POVIDONE IODINE
OINTMENT
10% Povidone Iodine, USP
(equivalent to 1% titratable iodine)

- First Aid Antiseptic
- For Hospital and Professional Use Only

Triad Group, Inc.
300 West North Shore Drive
Hartland, WI 53029
www.triad-group.net
Net Wt. 1 gram